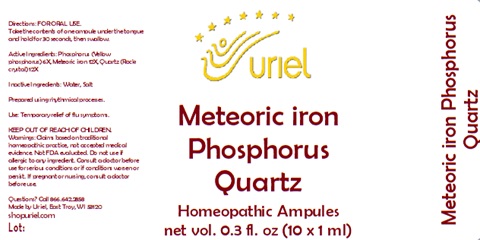 DRUG LABEL: Meteoric Iron Phosphorus Quartz
NDC: 48951-7051 | Form: LIQUID
Manufacturer: Uriel Pharmacy Inc.
Category: homeopathic | Type: HUMAN OTC DRUG LABEL
Date: 20240625

ACTIVE INGREDIENTS: PHOSPHORUS 6 [hp_X]/1 mL; IRON 12 [hp_X]/1 mL; SILICON DIOXIDE 12 [hp_X]/1 mL
INACTIVE INGREDIENTS: WATER; SODIUM CHLORIDE

Meteoric Iron Phosphorus Quartz

INDICATIONS AND USAGE

Directions: FOR ORAL USE.

DOSAGE AND ADMINISTRATION

Take the contents of one ampule under the tongue and hold for 30 seconds, then swallow.

ACTIVE INGREDIENT

Active Ingredients: Phosphorus (Yellow phosphorus) 6X, Meteoric iron 12X, Quartz (Rock crystal) 12X

Inactive Ingredients: Water, Salt

Prepared using rhythmical processes.

PURPOSE

Use: Temporary relief of flu symptoms.

KEEP OUT OF REACH OF CHILDREN.

WARNINGS

Warnings: Claims based on traditional homeopathic practice, not accepted medical evidence. Not FDA evaluated. Do not use if allergic to any ingredient. Consult a doctor before use for serious conditions or if conditions worsen or persist. If pregnant or nursing, consult a doctor before use.

QUESTIONS

Questions? Call 866.642.2858 Made by Uriel, East Troy, WI 53120 shopuriel.com Lot: